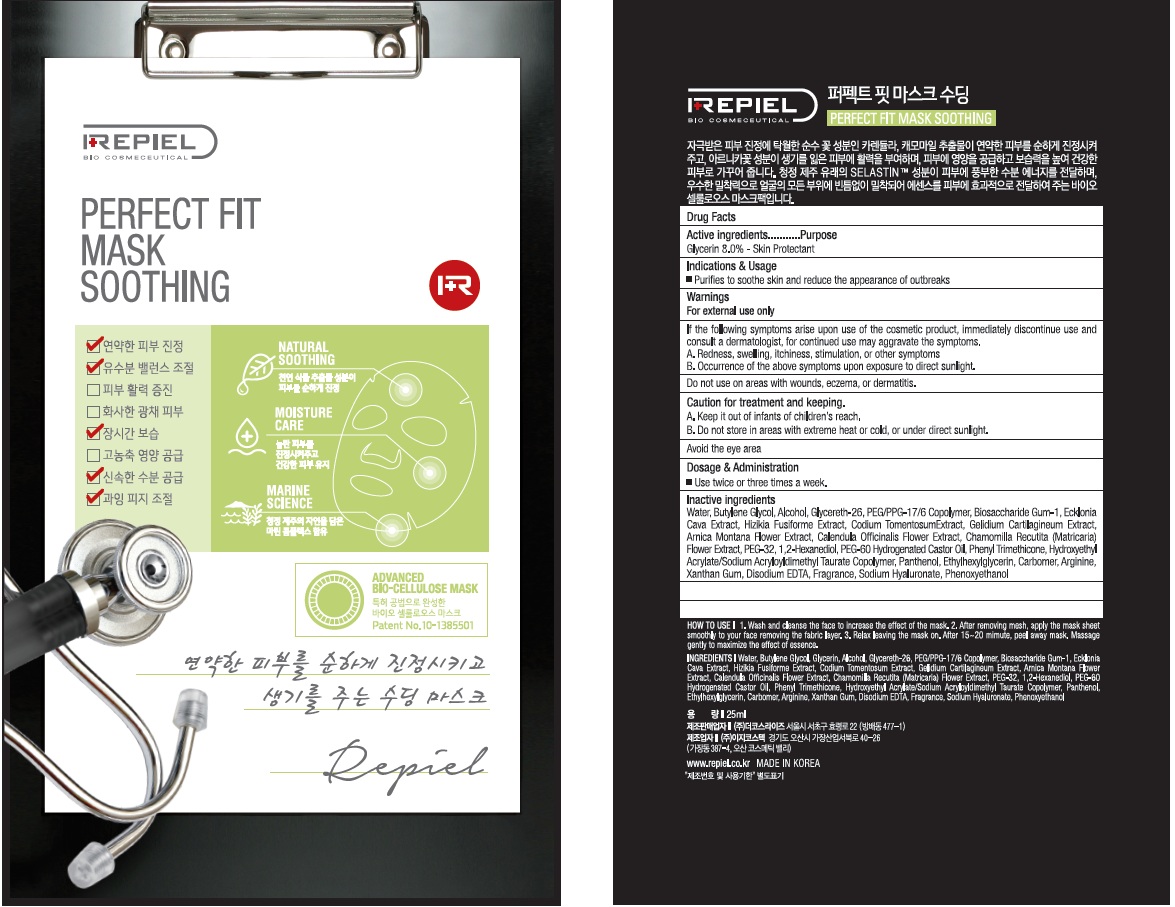 DRUG LABEL: REPIEL PERFECT FIT MASK SOOTHING
NDC: 70758-110 | Form: PATCH
Manufacturer: THE COSRISE CO.,LTD
Category: otc | Type: HUMAN OTC DRUG LABEL
Date: 20160630

ACTIVE INGREDIENTS: Glycerin 2 g/25 mL
INACTIVE INGREDIENTS: Water; Butylene Glycol

ACTIVE INGREDIENT

Active Ingredient: Glycerin 8.0%

INACTIVE INGREDIENT

Inactive Ingredients: Water, Butylene Glycol, Alcohol, Glycereth-26, PEG/PPG-17/6 Copolymer, Biosaccharide Gum-1, Ecklonia Cava Extract, Hizikia Fusiforme Extract, Codium TomentosumExtract, Gelidium Cartilagineum Extract, Arnica Montana Flower Extract, Calendula Officinalis Flower Extract, Chamomilla Recutita (Matricaria) Flower Extract, PEG-32, 1,2-Hexanediol, PEG-60 Hydrogenated Castor Oil, Phenyl Trimethicone, Hydroxyethyl Acrylate/Sodium Acryloyldimethyl Taurate Copolymer, Panthenol, Ethylhexylglycerin, Carbomer,Arginine, Xanthan Gum, Disodium EDTA, Fragrance, Sodium Hyaluronate, Phenoxyethanol

PURPOSE

Purpose: Skin Protectant

WARNINGS

Warnings: For external use only. 1. If the following symptoms arise upon use of the cosmetic product, immediately discontinue use and consult a dermatologist, for continued use may aggravate the symptoms. A. Redness, swelling, itchiness, stimulation, or other symptoms B. Occurrence of the above symptoms upon exposure to direct sunlight. 2. Do not use on areas with wounds, eczema, or dermatitis. 3. Caution for treatment and keeping. A. Keep it out of infants of children's reach. B. Do not store in areas with extreme heat or cold, or under direct sunlight. 4. Avoid the eye area

KEEP OUT OF REACH OF CHILDREN

Keep it out of infants of children's reach.

INDICATIONS & USAGE

Indications & Usage: Purifies to soothe skin and reduce the appearance of outbreaks. 1. Wash and cleanse the face to increase the effect of the mask 2. After removing mesh, apply the mask sheet smoothly to your face removing the fabric layer 3. Relax leaving the mask on, After 15~20 minute, peel away mask. Massage gently to maximize the effect of essence

DOSAGE & ADMINISTRATION

Dosage & Administration: Use twice or three times a week.